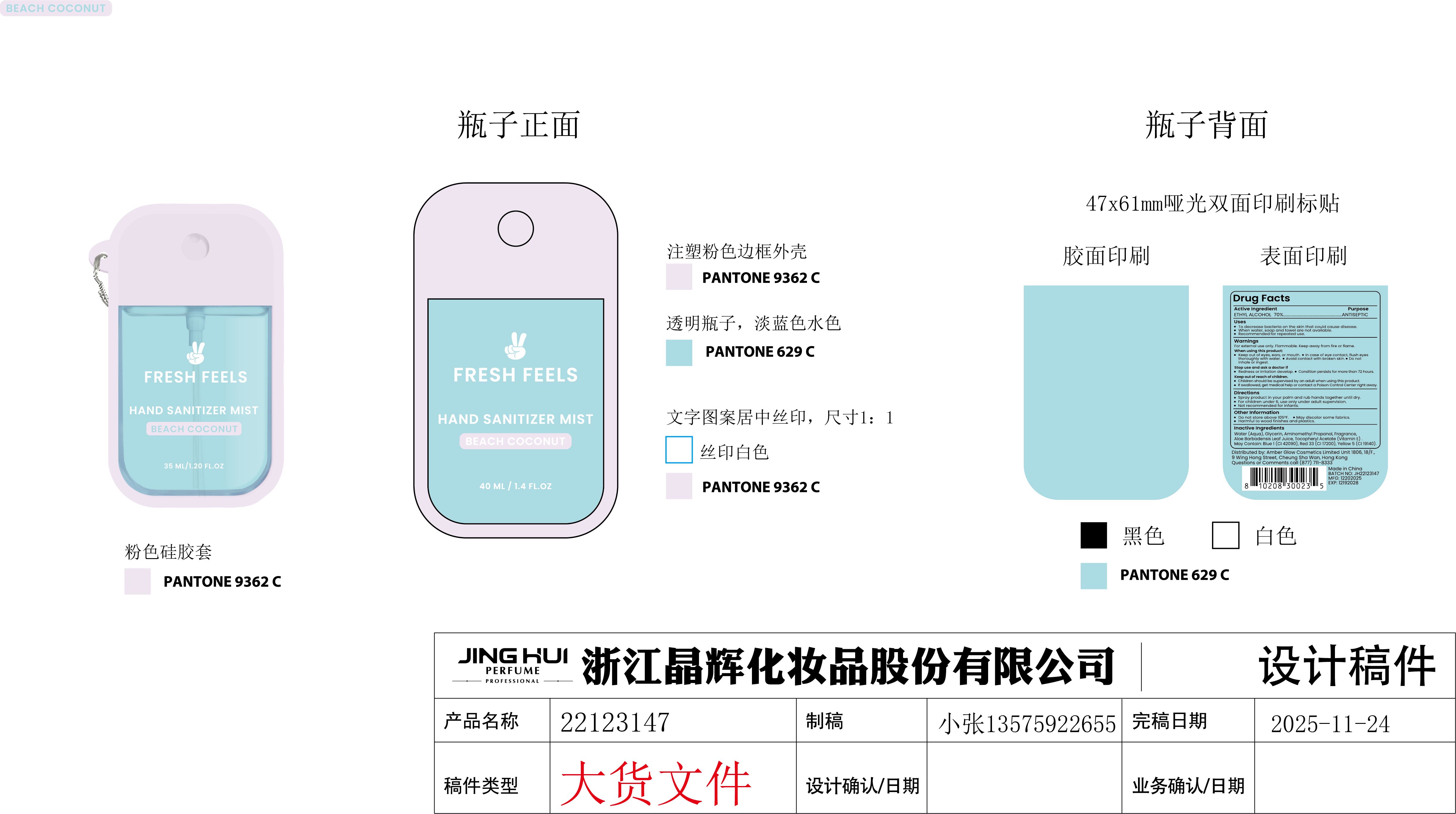 DRUG LABEL: FF SILICONE SPRY SANI PPK
NDC: 73905-046 | Form: LIQUID
Manufacturer: ZHEJIANG JINGHUI COSMETICS SHARE CO.,LTD
Category: otc | Type: HUMAN OTC DRUG LABEL
Date: 20251127

ACTIVE INGREDIENTS: ALCOHOL 70 mL/100 mL
INACTIVE INGREDIENTS: GLYCERIN; WATER; RED 33; BLUE 1; YELLOW 5; ALPHA-TOCOPHEROL ACETATE; AMINOMETHYL PROPANOL; ALOE BARBADENSIS LEAF JUICE

73905-046-01 FF SILICONE SPRY SANI PPK 40ml

Active Ingredients

ETHYL ALCOHOL 70% v/v

Purpose

ANTISEPTIC

Use

- To decrease bacteria on the skin that could cause disease.
- When water, soap and towel are not available.
- Recommended for repeated use.

Warnings

For external use only. Flammable, Keep away from fire or flame.

Do not use it near eye area. In case of contact, rinse eyes thoroughly with water.

WHEN USING

- Keep out of eyes, ears, or mouth.
- In case of eye contact, flush eyes thoroughly with water.
- Avoid contact with broken skin.
- Do not inhale or ingest.

Stop use and ask a doctor if
Redness of irritation develop.
Condition persists for more than 72 hours.

Keep out of reach of children.
Children should be supervised by an aduit when using this product.
If swallowed, get medical help or contact a Poison Control Center right away.

Directions

- Spray product in your palm and rub hands together until dry.
- For children under 6, use only under adult supervision.
- Not recommended for infants.

Other information

- Do not store above 105℉.
- May discolor some fabrics.
- Harmful to wood finishes and plastics.

Inactive ingredients

Water (Aqua), Glycerin, Aminomethyl Propanol, Fragrance, Aloe Barbadensis Leaf Juice, Tocopheryl Acetate (Vitamin E). May Contain: Blue 1 (CI 42090), Red 33 (CI 17200), Yellow 5 (CI 19140).

PACKAGE LABEL

40mL 73905-046-01